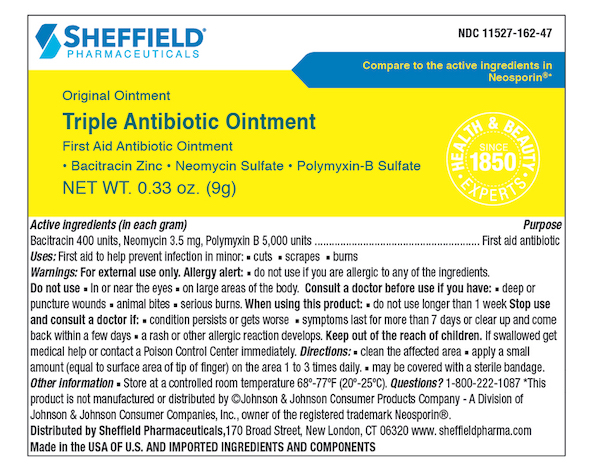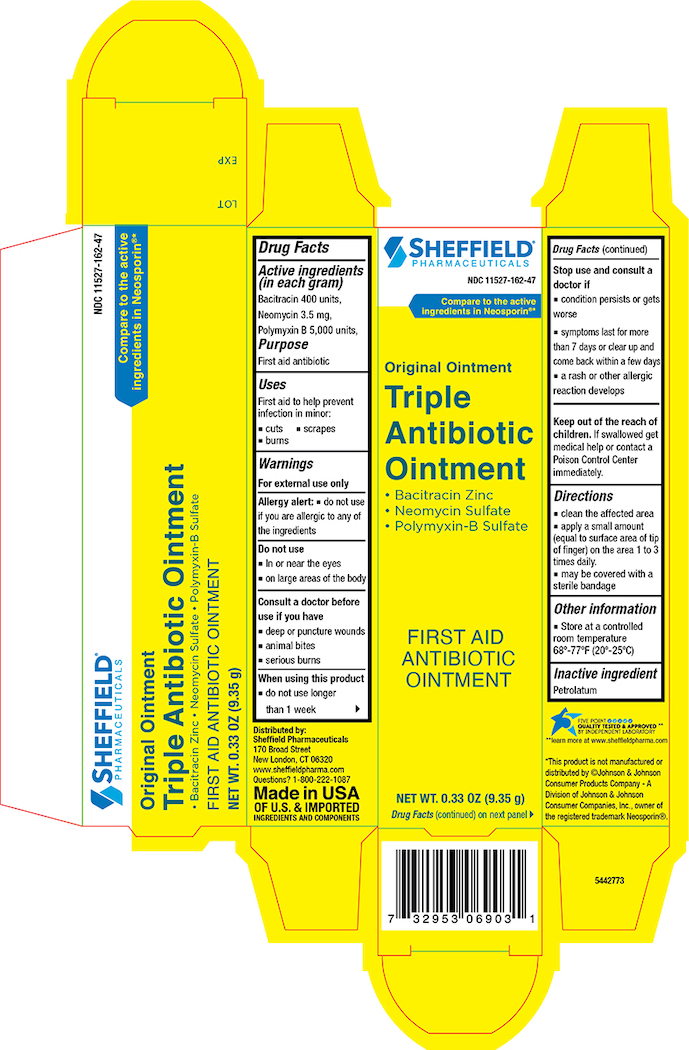 DRUG LABEL: Sheffield Triple Antibiotic
NDC: 11527-162 | Form: OINTMENT
Manufacturer: Sheffield Pharmaceuticals LLC
Category: otc | Type: HUMAN OTC DRUG LABEL
Date: 20250217

ACTIVE INGREDIENTS: Bacitracin Zinc 400 [USP'U]/1 g; Polymyxin B Sulfate 5000 [USP'U]/1 g; Neomycin Sulfate 3.5 mg/1 g
INACTIVE INGREDIENTS: Petrolatum

Sheffield Triple Antibiotic Ointment

Drug Facts

Active ingredients (In each gram)

Bacitracin 400

Neomycin 3.5 mg

Polymyxin B 5,000 units

Purpose

First aid antibiotic

First aid antibiotic

First aid antibiotic

Uses

First aid to help prevent infection in minor:

- cuts
- scrapes
- burns

Warnings

For external use only

Allergy alert:

- do not use if you are allergic to any of the ingredients

Do not use

- in or near the eyes
- on large areas of the body

Consult a doctor before use if you have

- deep or puncture wounds
- animal bites
- serious burns

When using this product

- do not use longer than 1 week

Stop use and consult a doctor if

- condition persists or gets worse
- symptoms last for more than 7 days or clear up and come back within a few days
- a rash or other allergic reaction develops

KEEP OUT OF REACH OF CHILDREN

Keep out of the reach of children. If swallowed get medical help or contact a Poison Control Center immediately.

Directions

- clean the affected area
- apply a small amount (equal to surface area of tip of finger) on the area 1 to 3 times daily.
- may be covered with a sterile bandage

Other information

- Store at a controlled room temperature 68º-77ºF (20º-25ºC)

Inactive ingredient

Petrolatum

Principal Display Panel – Carton Label

Dr. Sheffield's NDC 11527-162-47

Triple Antibiotic Ointment
Bacitracin Zinc • Neomycin Sulfate • Polymyxin-B Sulfate
First Aid Antibiotic Ointment

NET WT. 0.33 oz. (9.35)

Principal Display Panel – Tube Label

Dr. Sheffield's NDC 11527-162-47

Triple Antibiotic Ointment
Bacitracin Zinc • Neomycin Sulfate • Polymyxin-B Sulfate
First Aid Antibiotic Ointment

NET WT. 0.33 oz. (9.35g)
First Aid Treatment for Minor Cuts, Scrapes and Burns